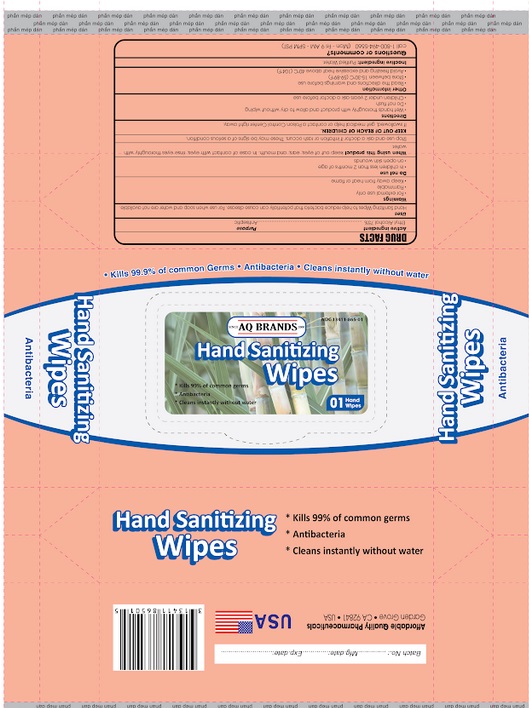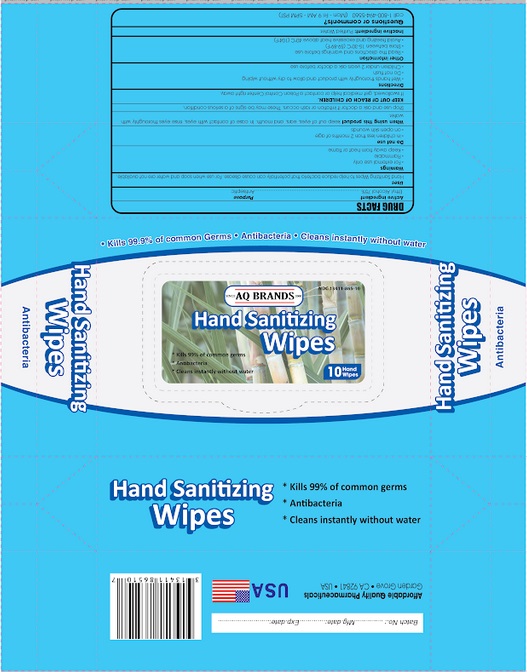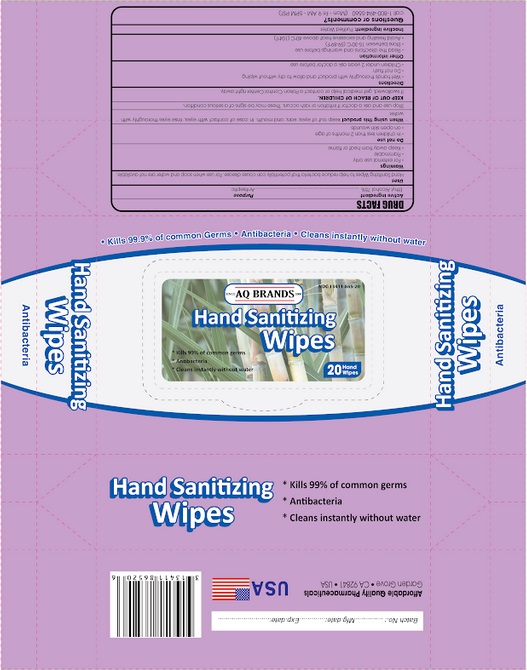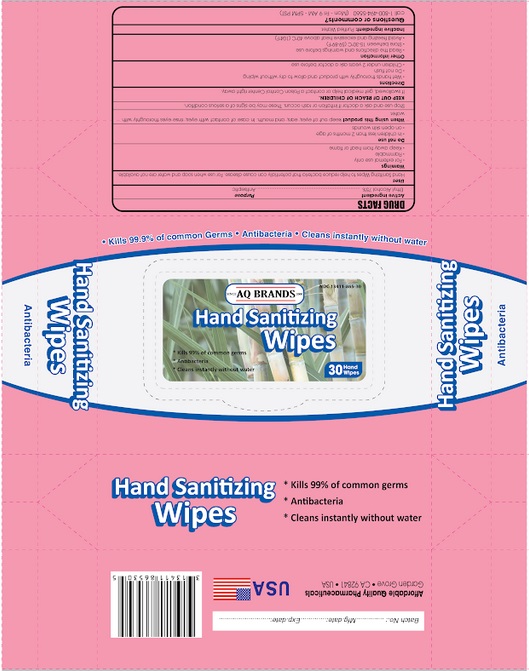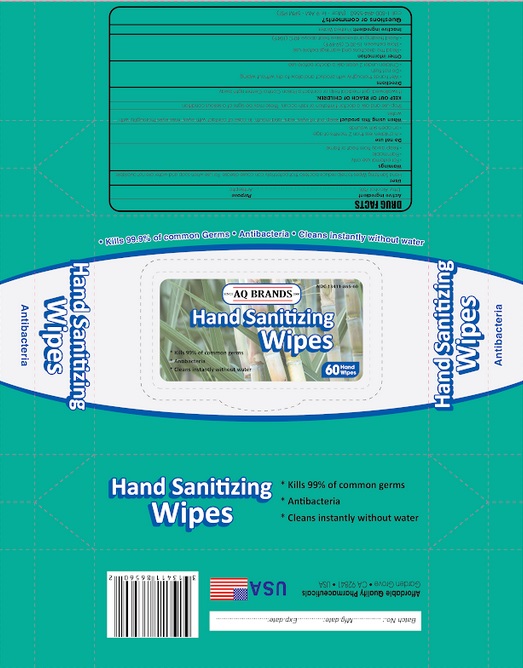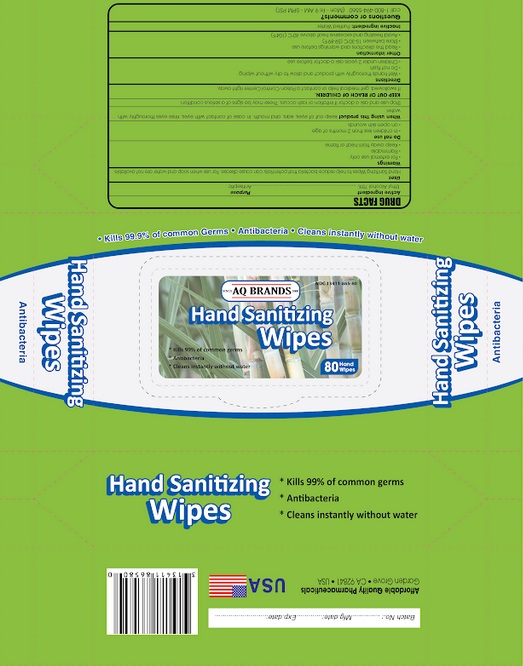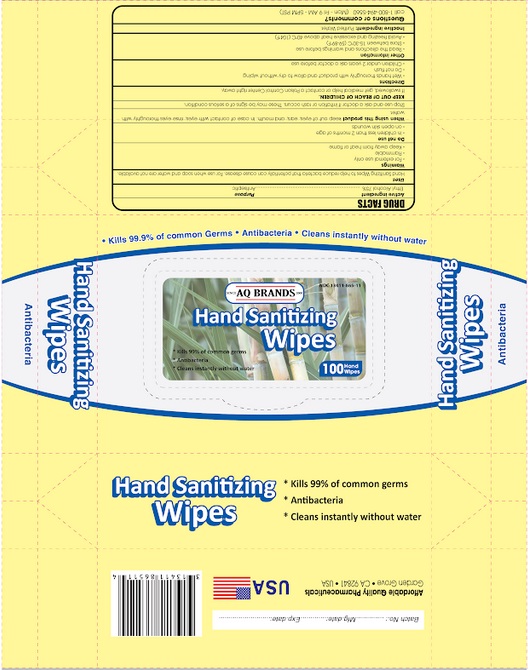 DRUG LABEL: AQ BRANDS hand sanitizing wipes
NDC: 13411-865 | Form: CLOTH
Manufacturer: Advanced Pharmaceutical Services, Inc. Dba Affordable Quality Pharmaceuticals
Category: otc | Type: HUMAN OTC DRUG LABEL
Date: 20200720

ACTIVE INGREDIENTS: ALCOHOL 75 mL/100 mL
INACTIVE INGREDIENTS: WATER

Active Ingredient

Ethyl Alcohol 75% v/v

Purpose

Antiseptic

Use

Hand Sanitizing wipe to help reduce bacteria that potentially can cause disease. For use when soap and water are not available.

Warnings

For external use only.

Flammable. Keep away from heat or flame.

Do not use

- in children less than 2 months of age
- on open skin wounds

When using this product keep out of eyes, ears, and mouth. In case of contact with eyes, rinse eyes thoroughly with water.

Stop use and ask a doctor if irritation or rash occurs. These may be signs of a serious condition.

Keep out of reach of children. If swallowed, get medical help or contact a Poison Control Center right away.

Directions

- Wet hands thoroughly with product and allow to dry without wiping.
- Do not flush.
- Children under 2 years of age, ask a doctor before use.

Other information

- Read the directions and warnings before use
- Store between 15-30C (59-86F)
- Avoid freezing and excessive heat above 40C (104F)

Inactive ingredients

purified water

Questions or Comments?

Call 1-800-494-5560 (Mon-Fri 9am-5pm PST)